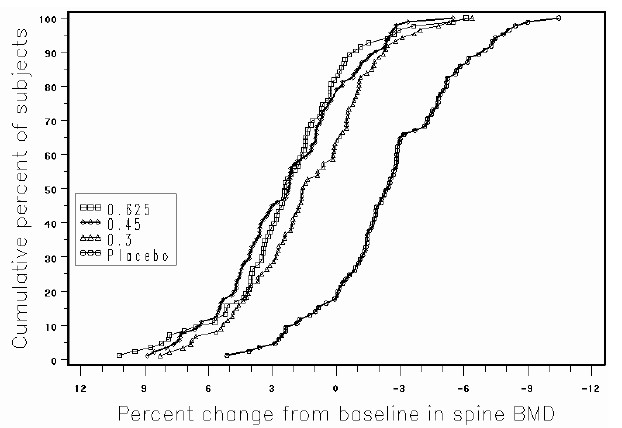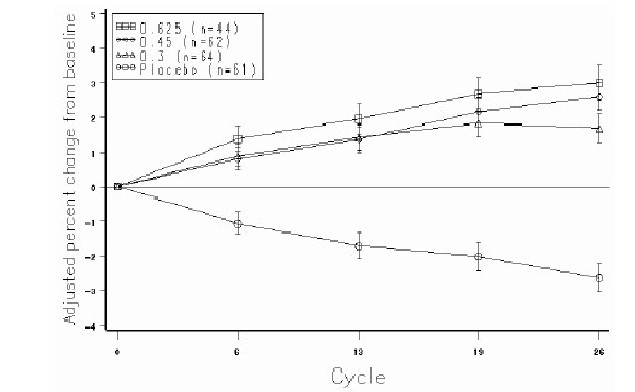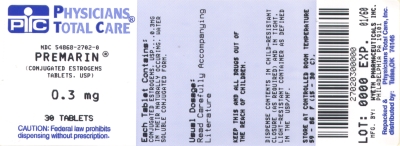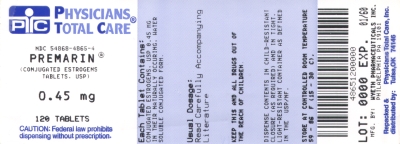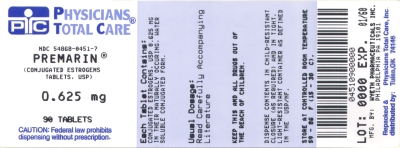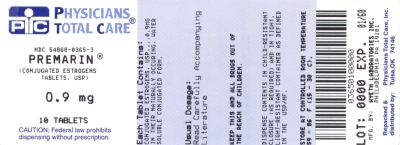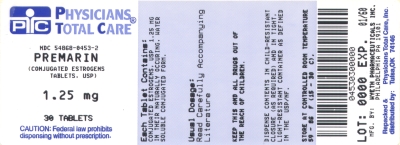 DRUG LABEL: Premarin
NDC: 54868-2702 | Form: TABLET, FILM COATED
Manufacturer: Physicians Total Care, Inc.
Category: prescription | Type: HUMAN PRESCRIPTION DRUG LABEL
Date: 20140508

ACTIVE INGREDIENTS: ESTROGENS, CONJUGATED 0.3 mg/1 1
INACTIVE INGREDIENTS: TRIBASIC CALCIUM PHOSPHATE; HYDROXYPROPYL CELLULOSE; CELLULOSE, MICROCRYSTALLINE; POWDERED CELLULOSE; HYPROMELLOSE 2208 (15000 MPA.S); HYPROMELLOSE 2910 (6 MPA.S); HYPROMELLOSE 2910 (15 MPA.S); LACTOSE MONOHYDRATE; POLYETHYLENE GLYCOL 400; SUCROSE; TITANIUM DIOXIDE; D&C YELLOW NO. 10; FD&C BLUE NO. 2

WARNINGS

ENDOMETRIAL CANCER

Adequate diagnostic measures, including endometrial sampling when indicated, should be undertaken to rule out malignancy in all cases of undiagnosed persistent or recurring abnormal vaginal bleeding. (See WARNINGS, Malignant neoplasms, Endometrial cancer.)

CARDIOVASCULAR AND OTHER RISKS

Estrogens with or without progestins should not be used for the prevention of cardiovascular disease or dementia. (See CLINICAL STUDIES and WARNINGS, Cardiovascular disorders and Dementia.)

The estrogen alone substudy of the Women's Health Initiative (WHI) reported increased risks of stroke and deep vein thrombosis (DVT) in postmenopausal women (50 to 79 years of age) during 6.8 years and 7.1 years, respectively, of treatment with daily oral conjugated estrogens (CE 0.625 mg), relative to placebo. (See CLINICAL STUDIES and WARNINGS, Cardiovascular disorders.)

The estrogen plus progestin substudy of WHI reported increased risks of myocardial infarction, stroke, invasive breast cancer, pulmonary emboli, and DVT in postmenopausal women (50 to 79 years of age) during 5.6 years of treatment with daily CE 0.625 mg combined with medroxyprogesterone acetate (MPA 2.5 mg), relative to placebo. (See CLINICAL STUDIES and WARNINGS, Cardiovascular disorders and Malignant neoplasms, Breast cancer.)

The Women's Health Initiative Memory Study (WHIMS), a substudy of WHI, reported an increased risk of developing probable dementia in postmenopausal women 65 years of age or older during 5.2 years of treatment with daily CE 0.625 mg alone and during 4 years of treatment with daily CE 0.625 mg combined with MPA 2.5 mg, relative to placebo. It is unknown whether this finding applies to younger postmenopausal women. (See CLINICAL STUDIES and WARNINGS, Dementia and PRECAUTIONS, Geriatric Use.)

In the absence of comparable data, these risks should be assumed to be similar for other doses of CE and MPA and other combinations and dosage forms of estrogens and progestins. Because of these risks, estrogens with or without progestins should be prescribed at the lowest effective doses and for the shortest duration consistent with treatment goals and risks for the individual woman.

DESCRIPTION

PREMARIN® (conjugated estrogens tablets, USP) for oral administration contains a mixture of conjugated estrogens obtained exclusively from natural sources, occurring as the sodium salts of water-soluble estrogen sulfates blended to represent the average composition of material derived from pregnant mares' urine. It is a mixture of sodium estrone sulfate and sodium equilin sulfate. It contains as concomitant components, as sodium sulfate conjugates, 17α-dihydroequilin, 17α-estradiol, and 17β-dihydroequilin. Tablets for oral administration are available in 0.3 mg, 0.45 mg, 0.625 mg, 0.9 mg, and 1.25 mg strengths of conjugated estrogens.

PREMARIN 0.3 mg, 0.45 mg, 0.625 mg, 0.9 mg, and 1.25 mg tablets also contain the following inactive ingredients: calcium phosphate tribasic, hydroxypropyl cellulose, microcrystalline cellulose, powdered cellulose, hypromellose, lactose monohydrate, magnesium stearate, polyethylene glycol, sucrose, and titanium dioxide.

— 0.3 mg tablets also contain: D&C Yellow No. 10 and FD&C Blue No. 2.

— 0.45 mg tablets also contain: FD&C Blue No. 2.

— 0.625 mg tablets also contain: FD&C Blue No. 2 and FD&C Red No. 40.

— 0.9 mg tablets also contain: D&C Red No. 30 and D&C Red No. 7.

— 1.25 mg tablets also contain: black iron oxide, D&C Yellow No. 10 and FD&C Yellow No. 6.

PREMARIN tablets comply with USP Dissolution Test criteria as outlined below:

PREMARIN 1.25 mg tablets | USP Dissolution Test 4
PREMARIN 0.3 mg, 0.45 mg and 0.625 mg tablets | USP Dissolution Test 5
PREMARIN 0.9 mg tablets | USP Dissolution Test 6

CLINICAL PHARMACOLOGY

Endogenous estrogens are largely responsible for the development and maintenance of the female reproductive system and secondary sexual characteristics. Although circulating estrogens exist in a dynamic equilibrium of metabolic interconversions, estradiol is the principal intracellular human estrogen and is substantially more potent than its metabolites, estrone and estriol, at the receptor level.

The primary source of estrogen in normally cycling adult women is the ovarian follicle, which secretes 70 to 500 mcg of estradiol daily, depending on the phase of the menstrual cycle. After menopause, most endogenous estrogen is produced by conversion of androstenedione, secreted by the adrenal cortex, to estrone by peripheral tissues. Thus, estrone and the sulfate-conjugated form, estrone sulfate, are the most abundant circulating estrogens in postmenopausal women.

Estrogens act through binding to nuclear receptors in estrogen-responsive tissues. To date, two estrogen receptors have been identified. These vary in proportion from tissue to tissue.

Circulating estrogens modulate the pituitary secretion of the gonadotropins, luteinizing hormone (LH) and follicle stimulating hormone (FSH), through a negative feedback mechanism. Estrogens act to reduce the elevated levels of these gonadotropins seen in postmenopausal women.

Pharmacokinetics

A. Absorption

Conjugated estrogens are water-soluble and are well-absorbed from the gastrointestinal tract after release from the drug formulation. The PREMARIN tablet releases conjugated estrogens slowly over several hours. Table 1 summarizes the mean pharmacokinetic parameters for unconjugated and conjugated estrogens following administration of 1 x 0.625 mg and 1 x 1.25 mg tablets to healthy postmenopausal women.

The pharmacokinetics of PREMARIN 0.45 mg and 1.25 mg tablets were assessed following a single dose with a high-fat breakfast and with fasting administration. The Cmax and AUC of estrogens were altered approximately 3-13%. The changes to Cmax and AUC are not considered clinically meaningful.

TABLE 1. PHARMACOKINETIC PARAMETERS FOR PREMARIN®
Pharmacokinetic Profile of Unconjugated Estrogens Following a Dose of 1 x 0.625 mg
PK Parameter Arithmetic Mean (%CV) | Cmax (pg/mL) | tmax (h) | t1/2 (h) | AUC (pg•h/mL)
Estrone | 87 (33) | 9.6 (33) | 50.7 (35) | 5557 (59)
Baseline-adjusted estrone | 64 (42) | 9.6 (33) | 20.2 (40) | 1723 (52)
Equilin | 31 (38) | 7.9 (32) | 12.9 (112) | 602 (54)
Pharmacokinetic Profile of Conjugated Estrogens Following a Dose of 1 x 0.625 mg
PK Parameter Arithmetic Mean (%CV) | Cmax (ng/mL) | tmax (h) | t1/2 (h) | AUC (ng•h/mL)
Total Estrone | 2.7 (43) | 6.9 (25) | 26.7 (33) | 75 (52)
Baseline-adjusted total estrone | 2.5 (45) | 6.9 (25) | 14.8 (35) | 46 (48)
Total Equilin | 1.8 (56) | 5.6 (45) | 11.4 (31) | 27 (56)
Pharmacokinetic Profile of Unconjugated Estrogens Following a Dose of 1 x 1.25 mg
PK Parameter Arithmetic Mean (%CV) | Cmax (pg/mL) | tmax (h) | t1/2 (h) | AUC (pg•h/mL)
Estrone | 124 (30) | 10.0 (32) | 38.1 (37) | 6332 (44)
Baseline-adjusted estrone | 102 (35) | 10.0 (32) | 19.7 (48) | 3159 (53)
Equilin | 59 (43) | 8.8 (36) | 10.9 (47) | 1182 (42)
Pharmacokinetic Profile of Conjugated Estrogens Following a Dose of 1 x 1.25 mg
PK Parameter Arithmetic Mean (%CV) | Cmax (ng/mL) | tmax (h) | t1/2 (h) | AUC (ng•h/mL)
Total Estrone | 4.5 (39) | 8.2 (58) | 26.5 (40) | 109 (46)
Baseline-adjusted total estrone | 4.3 (41) | 8.2 (58) | 17.5 (41) | 87 (44)
Total equilin | 2.9 (42) | 6.8 (49) | 12.5 (34) | 48 (51)

B. Distribution

The distribution of exogenous estrogens is similar to that of endogenous estrogens. Estrogens are widely distributed in the body and are generally found in higher concentration in the sex hormone target organs. Estrogens circulate in the blood largely bound to sex hormone binding globulin (SHBG) and albumin.

C. Metabolism

Exogenous estrogens are metabolized in the same manner as endogenous estrogens. Circulating estrogens exist in a dynamic equilibrium of metabolic interconversions. These transformations take place mainly in the liver. Estradiol is converted reversibly to estrone, and both can be converted to estriol, which is the major urinary metabolite. Estrogens also undergo enterohepatic recirculation via sulfate and glucuronide conjugation in the liver, biliary secretion of conjugates into the intestine, and hydrolysis in the intestine followed by reabsorption. In postmenopausal women a significant proportion of the circulating estrogens exists as sulfate conjugates, especially estrone sulfate, which serves as a circulating reservoir for the formation of more active estrogens.

D. Excretion

Estradiol, estrone, and estriol are excreted in the urine, along with glucuronide and sulfate conjugates.

E. Special Populations

No pharmacokinetic studies were conducted in special populations, including patients with renal or hepatic impairment.

F. Drug Interactions

Data from a single-dose drug-drug interaction study involving conjugated estrogens and medroxyprogesterone acetate indicate that the pharmacokinetic dispositions of both drugs are not altered when the drugs are coadministered. No other clinical drug-drug interaction studies have been conducted with conjugated estrogens.

In vitro and in vivo studies have shown that estrogens are metabolized partially by cytochrome P450 3A4 (CYP3A4). Therefore, inducers or inhibitors of CYP3A4 may affect estrogen drug metabolism. Inducers of CYP3A4, such as St. John's Wort preparations (Hypericum perforatum), phenobarbital, carbamazepine, and rifampin, may reduce plasma concentrations of estrogens, possibly resulting in a decrease in therapeutic effects and/or changes in the uterine bleeding profile. Inhibitors of CYP3A4, such as erythromycin, clarithromycin, ketoconazole, itraconazole, ritonavir and grapefruit juice, may increase plasma concentrations of estrogens and may result in side effects.

CLINICAL STUDIES

Effects on vasomotor symptoms

In the first year of the Health and Osteoporosis, Progestin and Estrogen (HOPE) Study, a total of 2,805 postmenopausal women (average age 53.3 ± 4.9 years) were randomly assigned to one of eight treatment groups, receiving either placebo or conjugated estrogens, with or without medroxyprogesterone acetate. Efficacy for vasomotor symptoms was assessed during the first 12 weeks of treatment in a subset of symptomatic women (n = 241) who had at least seven moderate to severe hot flushes daily, or at least 50 moderate to severe hot flushes during the week before randomization. PREMARIN (0.3 mg, 0.45 mg, and 0.625 mg tablets) was shown to be statistically better than placebo at weeks 4 and 12 for relief of both the frequency and severity of moderate to severe vasomotor symptoms. Table 2 shows the adjusted mean number of hot flushes in the PREMARIN 0.3 mg, 0.45 mg, and 0.625 mg and placebo treatment groups over the initial 12-week period.

TABLE 2. SUMMARY TABULATION OF THE NUMBER OF HOT FLUSHES PER DAY – MEAN VALUES AND COMPARISONS BETWEEN THE ACTIVE TREATMENT GROUPS AND THE PLACEBO GROUP: PATIENTS WITH AT LEAST 7 MODERATE TO SEVERE FLUSHES PER DAY OR AT LEAST 50 PER WEEK AT BASELINE, LAST OBSERVATION CARRIED FORWARD (LOCF)
Treatment (No. of Patients)
Time Period | Baseline | Observed | Mean | p-Values
(week) | Mean ± SD | Mean ± SD | Change ± SD | vs. Placeboa
0.625 mg CE (n = 27)
4 | 12.29 ± 3.89 | 1.95 ± 2.77 | -10.34 ± 4.73 | less than 0.001
12 | 12.29 ± 3.89 | 0.75 ± 1.82 | -11.54 ± 4.62 | less than 0.001
0.45 mg CE (n = 32)
4 | 12.25 ± 5.04 | 5.04 ± 5.31 | -7.21 ± 4.75 | less than 0.001
12 | 12.25 ± 5.04 | 2.32 ± 3.32 | -9.93 ± 4.64 | less than 0.001
0.3 mg CE (n = 30)
4 | 13.77 ± 4.78 | 4.65 ± 3.71 | -9.12 ± 4.71 | less than 0.001
12 | 13.77 ± 4.78 | 2.52 ± 3.23 | -11.25 ± 4.60 | less than 0.001
Placebo (n = 28)
4 | 11.69 ± 3.87 | 7.89 ± 5.28 | -3.80 ± 4.71 | -
12 | 11.69 ± 3.87 | 5.71 ± 5.22 | -5.98 ± 4.60 | -

a: Based on analysis of covariance with treatment as factor and baseline as covariate.
Effects on vulvar and vaginal atrophy

Results of vaginal maturation indexes at cycles 6 and 13 showed that the differences from placebo were statistically significant (p less than 0.001) for all treatment groups (conjugated estrogens alone and conjugated estrogens/medroxyprogesterone acetate treatment groups).

Effects on bone mineral density

Health and Osteoporosis, Progestin and Estrogen HOPE) Study

The HOPE study was a double-blind, randomized, placebo/active-drug-controlled, multicenter study of healthy postmenopausal women with an intact uterus. Subjects (mean age 53.3 ± 4.9 years) were 2.3 ± 0.9 years on average since menopause and took one 600-mg tablet of elemental calcium (Caltrate™) daily. Subjects were not given Vitamin D supplements. They were treated with PREMARIN 0.625 mg, 0.45 mg, 0.3 mg, or placebo. Prevention of bone loss was assessed by measurement of bone mineral density (BMD), primarily at the anteroposterior lumbar spine (L2 to L4). Secondarily, BMD measurements of the total body, femoral neck, and trochanter were also analyzed. Serum osteocalcin, urinary calcium, and N-telopeptide were used as bone turnover markers (BTM) at cycles 6, 13, 19, and 26.

Intent-to-treat subjects

All active treatment groups showed significant differences from placebo in each of the four BMD endpoints at cycles 6, 13, 19, and 26. The mean percent increases in the primary efficacy measure (L2 to L4 BMD) at the final on‑therapy evaluation (cycle 26 for those who completed and the last available evaluation for those who discontinued early) were 2.46 percent with 0.625 mg, 2.26 percent with 0.45 mg, and 1.13 percent with 0.3 mg. The placebo group showed a mean percent decrease from baseline at the final evaluation of 2.45 percent. These results show that the lower dosages of PREMARIN were effective in increasing L2 to L4 BMD compared with placebo, and therefore support the efficacy of the lower doses.

The analysis for the other three BMD endpoints yielded mean percent changes from baseline in femoral trochanter that were generally larger than those seen for L2 to L4, and changes in femoral neck and total body that were generally smaller than those seen for L2 to L4. Significant differences between groups indicated that each of the PREMARIN treatments was more effective than placebo for all three of these additional BMD endpoints. With regard to femoral neck and total body, the active treatment groups all showed mean percent increases in BMD, while placebo treatment was accompanied by mean percent decreases. For femoral trochanter, each of the PREMARIN dose groups showed a mean percent increase that was significantly greater than the small increase seen in the placebo group. The percent changes from baseline to final evaluation are shown in Table 3.

TABLE 3. PERCENT CHANGE IN BONE MINERAL DENSITY: COMPARISON BETWEEN ACTIVE AND PLACEBO GROUPS IN THE INTENT-TO-TREAT POPULATION, LOCF
Region Evaluated Treatment Groupa | No. of Subjects | Baseline (g/cm^2) Mean ± SD | Change from Baseline (%) Adjusted Mean ± SE | p-Value vs Placebo
L2 to L4 BMD
0.625 | 83 | 1.17 ± 0.15 | 2.46 ± 0.37 | less than 0.001
0.45 | 91 | 1.13 ± 0.15 | 2.26 ± 0.35 | less than 0.001
0.3 | 87 | 1.14 ± 0.15 | 1.13 ± 0.36 | less than 0.001
Placebo | 85 | 1.14 ± 0.14 | -2.45 ± 0.36
Total Body BMD
0.625 | 84 | 1.15 ± 0.08 | 0.68 ± 0.17 | less than 0.001
0.45 | 91 | 1.14 ± 0.08 | 0.74 ± 0.16 | less than 0.001
0.3 | 87 | 1.14 ± 0.07 | 0.40 ± 0.17 | less than 0.001
Placebo | 85 | 1.13 ± 0.08 | -1.50 ± 0.17
Femoral Neck BMD
0.625 | 84 | 0.91 ± 0.14 | 1.82 ± 0.45 | less than 0.001
0.45 | 91 | 0.89 ± 0.13 | 1.84 ± 0.44 | less than 0.001
0.3 | 87 | 0.86 ± 0.11 | 0.62 ± 0.45 | less than 0.001
Placebo | 85 | 0.88 ± 0.14 | -1.72 ± 0.45
Femoral Trochanter BMD
0.625 | 84 | 0.78 ± 0.13 | 3.82 ± 0.58 | less than 0.001
0.45 | 91 | 0.76 ± 0.12 | 3.16 ± 0.56 | 0.003
0.3 | 87 | 0.75 ± 0.10 | 3.05 ± 0.57 | 0.005
Placebo | 85 | 0.75 ± 0.12 | 0.81 ± 0.58

a: Identified by dosage (mg) of PREMARIN or placebo.

Figure 1 shows the cumulative percentage of subjects with changes from baseline equal to or greater than the value shown on the x-axis.

Figure 1. CUMULATIVE PERCENT OF SUBJECTS WITH CHANGES FROM BASELINE IN SPINE BMD OF GIVEN MAGNITUDE OR GREATER IN PREMARIN® AND PLACEBO GROUPS

The mean percent changes from baseline in L2 to L4 BMD for women who completed the bone density study are shown with standard error bars by treatment group in Figure 2. Significant differences between each of the PREMARIN dosage groups and placebo were found at cycles 6, 13, 19, and 26.

Figure 2. ADJUSTED MEAN (SE) PERCENT CHANGE FROM BASELINE AT EACH CYCLE IN SPINE BMD: SUBJECTS COMPLETING IN PREMARIN® GROUPS AND PLACEBO

The bone turnover markers serum osteocalcin and urinary N-telopeptide significantly decreased (p less than 0.001) in all active-treatment groups at cycles 6, 13, 19, and 26 compared with the placebo group. Larger mean decreases from baseline were seen with the active groups than with the placebo group. Significant differences from placebo were seen less frequently in urine calcium.

Women's Health Initiative Studies

The Women's Health Initiative (WHI) enrolled approximately 27,000 predominantly healthy postmenopausal women in two substudies to assess the risks and benefits of either the use of daily oral conjugated estrogens (CE 0.625 mg) alone or in combination with medroxyprogesterone acetate (MPA 2.5 mg) compared to placebo in the prevention of certain chronic diseases. The primary endpoint was the incidence of coronary heart disease [CHD] (nonfatal myocardial infarction [MI], silent MI and CHD death), with invasive breast cancer as the primary adverse outcome. A “global index” included the earliest occurrence of CHD, invasive breast cancer, stroke, pulmonary embolism (PE), endometrial cancer (only in CE/MPA substudy),colorectal cancer, hip fracture, or death due to other causes. The study did not evaluate the effects of CE or CE/MPA on menopausal symptoms.

The estrogen alone substudy was stopped early because an increased risk of stroke was observed, and it was deemed that no further information would be obtained regarding the risks and benefits of estrogen alone in predetermined primary endpoints. Results of the estrogen alone substudy, which included 10,739 women (average age of 63 years, range 50 to 79; 75.3 percent White, 15.1 percent Black, 6.1 percent Hispanic, 3.6 percent Other) after an average follow-up of 6.8 years, are presented in Table 4.

TABLE 4. RELATIVE AND ABSOLUTE RISK SEEN IN THE ESTROGEN ALONE SUBSTUDY OF WHI
 | Relavtive Risk | Placebo n = 5,429 | CE n = 5,310
Event | CE vs. Placebo (95% nCIa) | Absolute Risk Women - | per 10,000 Years
CHD eventsb | 0.95 (0.79-1.16) | 56 | 53
Non-fatal MIb | 0.91 (0.73-1.14) | 43 | 40
CHD deathb | 1.01 (0.71-1.43) | 16 | 16
Strokeb | 1.37 (1.09-1.73) | 33 | 45
Ischemicb | 1.55 (1.19-2.01) | 25 | 38
Deep vein thrombosisb,d | 1.47 (1.06-2.06) | 15 | 23
Pulmonary embolismb | 1.37 (0.90-2.07) | 10 | 14
Invasive breast cancerb | 0.80 (0.62-1.04) | 34 | 28
Colorectal cancerc | 1.08 (0.75-1.55) | 16 | 17
Hip fracturec | 0.61 (0.41-0.91) | 17 | 11
Vertebral fracturesc,d | 0.62 (0.42-0.93) | 17 | 11
Total fracturesc,d | 0.70 (0.63-0.79) | 195 | 139
Death due to other causesc,e | 1.08 (0.88-1.32) | 50 | 53
Overall mortalityc,d | 1.04 (0.88-1.22) | 78 | 81
Global Indexc,f | 1.01 (0.91-1.12) | 190 | 192

a Nominal confidence intervals unadjusted for multiple looks and multiple comparisons.
b Results are based on centrally adjudicated data for an average follow-up of 7.1 years.
c Results are based on an average follow-up of 6.8 years.
d Not included in Global Index.
e All deaths, except from breast or colorectal cancer, definite/probable CHD, PE or cerebrovascular disease.
f A subset of the events was combined in a “global index,” defined as the earliest occurrence of CHD events, invasive breast cancer, stroke, pulmonary embolism, colorectal cancer, hip fracture, or death due to other causes.

For those outcomes included in the WHI “global index” that reached statistical significance, the absolute excess risk per 10,000 women-years in the group treated with CE alone were 12 more strokes while the absolute risk reduction per 10,000 women-years was 6 fewer hip fractures. The absolute excess risk of events included in the “global index” was a nonsignificant 2 events per 10,000 women-years. There was no difference between the groups in terms of all-cause mortality. (See BOXED WARNINGS, WARNINGS, and PRECAUTIONS.)

Final centrally adjudicated results for CHD events and centrally adjudicated results for invasive breast cancer incidence from the estrogen alone substudy, after an average follow-up of 7.1 years, reported no overall difference for primary CHD events (nonfatal MI, silent MI and CHD death) and invasive breast cancer incidence in women receiving CE alone compared with placebo (see Table 4).

Centrally adjudicated results for stroke events from the estrogen alone substudy, after an average follow-up of 7.1 years, reported no significant difference in distribution of stroke subtype or severity, including fatal strokes, in women receiving CE alone compared to placebo. Estrogen alone increased the risk of ischemic stroke, and this excess was present in all subgroups of women examined (see Table 4).

The estrogen plus progestin substudy was also stopped early. According to the predefined stopping rule, after an average follow-up of 5.2 years of treatment, the increased risk of breast cancer and cardiovascular events exceeded the specified benefits included in the “global index.” The absolute excess risk of events included in the “global index” was 19 per 10,000 women-years (relative risk [RR] 1.15, 95 percent nCI 1.03-1.28).

For those outcomes included in the WHI “global index” that reached statistical significance after 5.6 years of follow-up, the absolute excess risks per 10,000 women years in the group treated with CE/MPA were 6 more CHD events, 7 more strokes, 10 more PEs, and 8 more invasive breast cancers, while the absolute risk reductions per 10,000 women-years were 7 fewer colorectal cancers and 5 fewer hip fractures. (See BOXED WARNINGS, WARNINGS, and PRECAUTIONS.)

Results of the estrogen plus progestin substudy, which included 16,608 women (average age of 63 years, range 50 to 79; 83.9 percent White, 6.8 percent Black, 5.4 percent Hispanic, 3.9 percent Other), are presented in Table 5. These results reflect centrally adjudicated data after an average follow-up of 5.6 years.

TABLE 5. RELATIVE AND ABSOLUTE RISK SEEN IN THE ESTROGEN PLUS PROGESTIN SUBSTUDY OF WHI AT AN AVERAGE OF 5.6 YEARSa
 | Relative Risk | Placebo n = 8,102 | CE/MPA N = 8,506
Event | CE/MPA vs. Placebo (95% nCIb) | Absolute Risk Women - | per 10,000 years
CHD events | 1.24 (1.00-1.54) | 33 | 39
Non-fatal MI | 1.28 (1.00-1.63) | 25 | 31
CHD death | 1.10 (0.70-1.75) | 8 | 8
All strokes | 1.31 (1.02-1.68) | 24 | 31
Ischemic Stroke | 1.44 (1.09-1.90) | 18 | 26
Deep vein thrombosis | 1.95 (1.43-2.67) | 13 | 26
Pulmonary embolism | 2.13 (1.45-3.11) | 8 | 18
Invasive breast cancerc | 1.24 (1.01-1.54) | 33 | 41
Invasive colorectal cancer | 0.56 (0.38-0.81) | 16 | 9
Endometrial cancer | 0.81 (0.48-1.36) | 7 | 6
Cervical cancer | 1.44 (0.47-4.42) | 1 | 2
Hip fracture | 0.67 (0.47-0.96) | 16 | 11
Vertebral fractures | 0.65 (0.46-0.92) | 17 | 11
Lower arm/wrist fractures | 0.71 (0.59-0.85) | 62 | 44
Total fractures | 0.76 (0.69-0.83) | 199 | 152

a Results are based on centrally adjudicated data. Mortality data was not part of the adjudicated data; however, data at 5.2 years of follow-up showed no difference between the groups in terms of all-cause mortality (RR 0.98, 95 percent nCI 0.82-1.18).
b Nominal confidence intervals unadjusted for multiple looks and multiple comparisons.
c Includes metastatic and non-metastatic breast cancer, with the exception of in situ breast cancer.

Women's Health Initiative Memory Study

The estrogen alone Women's Health Initiative Memory Study (WHIMS), a substudy of WHI, enrolled 2,947 predominantly healthy postmenopausal women 65 years of age and older (45 percent, age 65 to 69 years; 36 percent, 70 to 74 years; 19 percent, 75 years of age and older) to evaluate the effects of daily CE 0.625 mg on the incidence of probable dementia (primary outcome) compared with placebo.

After an average follow-up of 5.2 years, 28 women in the estrogen alone group (37 per 10,000 women-years) and 19 in the placebo group (25 per 10,000 women-years) were diagnosed with probable dementia. The relative risk of probable dementia in the estrogen alone group was 1.49 (95 percent CI 0.83–2.66) compared to placebo. It is unknown whether these findings apply to younger postmenopausal women. (See BOXED WARNINGS, WARNINGS, Dementia and PRECAUTIONS, Geriatric Use.)

The estrogen plus progestin WHIMS substudy enrolled 4,532 predominantly healthy postmenopausal women 65 years of age and older (47 percent, age 65 to 69 years; 35 percent, 70 to 74 years; 18 percent, 75 years of age and older) to evaluate the effects of CE/MPA 0.625 mg conjugated estrogens/2.5 mg medroxyprogesterone acetate daily on the incidence of probable dementia (primary outcome) compared with placebo.

After an average follow-up of 4 years, 40 women in the estrogen plus progestin group (45 per 10,000 women-years) and 21 in the placebo group (22 per 10,000 women-years) were diagnosed with probable dementia. The relative risk of probable dementia in the hormone therapy group was 2.05 (95 percent CI 1.21–3.48) compared to placebo. It is unknown whether these findings apply to younger postmenopausal women. (See BOXED WARNINGS, WARNINGS, Dementia and PRECAUTIONS, Geriatric Use.)

When data from the two populations were pooled as planned in the WHIMS protocol, the reported overall relative risk for probable dementia was 1.76 (95 percent CI 1.19-2.60). Differences between groups became apparent in the first year of treatment. It is unknown whether these findings apply to younger postmenopausal women. (See BOXED WARNINGS, WARNINGS, Dementia and PRECAUTIONS, Geriatric Use.)

INDICATIONS AND USAGE

PREMARIN therapy is indicated in the:

1. Treatment of moderate to severe vasomotor symptoms due to menopause.
2. Treatment of moderate to severe symptoms of vulvar and vaginal atrophy due to menopause. When prescribing solely for the treatment of symptoms of vulvar and vaginal atrophy, topical vaginal products should be considered.
3. Treatment of hypoestrogenism due to hypogonadism, castration or primary ovarian failure.
4. Treatment of breast cancer (for palliation only) in appropriately selected women and men with metastatic disease.
5. Treatment of advanced androgen-dependent carcinoma of the prostate (for palliation only).
6. Prevention of postmenopausal osteoporosis. When prescribing solely for the prevention of postmenopausal osteoporosis, therapy should only be considered for women at significant risk of osteoporosis and for whom non-estrogen medications are not considered to be appropriate. (See CLINICAL STUDIES.)
  The mainstays for decreasing the risk of postmenopausal osteoporosis are weight-bearing exercise, adequate calcium and vitamin D intake, and when indicated, pharmacologic therapy. Postmenopausal women require an average of 1500 mg/day of elemental calcium. Therefore, when not contraindicated, calcium supplementation may be helpful for women with suboptimal dietary intake. Vitamin D supplementation of 400-800 IU/day may also be required to ensure adequate daily intake in postmenopausal women.

CONTRAINDICATIONS

PREMARIN therapy should not be used in individuals with any of the following conditions:

1. Undiagnosed abnormal genital bleeding.
2. Known, suspected, or history of cancer of the breast except in appropriately selected patients being treated for metastatic disease.
3. Known or suspected estrogen-dependent neoplasia.
4. Active deep vein thrombosis, pulmonary embolism or a history of these conditions.
5. Active or recent (within the past year) arterial thromboembolic disease (for example, stroke, myocardial infarction).
6. Liver dysfunction or disease.
7. Known hypersensitivity to any of the ingredients in PREMARIN.
8. Known or suspected pregnancy.

WARNINGS

See BOXED WARNINGS.

1. Cardiovascular disorders

An increased risk of stroke and deep vein thrombosis (DVT) has been reported with estrogen alone therapy.

An increased risk of stroke, DVT, pulmonary embolism, and myocardial infarction has been reported with estrogen plus progestin therapy.

Should any of these events occur or be suspected, estrogens with or without progestins should be discontinued immediately.

Risk factors for arterial vascular disease (for example, hypertension, diabetes mellitus, tobacco use, hypercholesterolemia, and obesity) and/or venous thromboembolism (for example, personal history or family history of VTE, obesity, and systemic lupus erythematosus) should be managed appropriately.

a. Stroke

In the Women's Health Initiative (WHI) estrogen alone substudy, a statistically significant increased risk of stroke was reported in women receiving daily conjugated estrogens (CE 0.625 mg) compared to placebo (44 versus 32 per 10,000 women-years). The increase in risk was demonstrated in year one and persisted. (See CLINICAL STUDIES.)

In the estrogen plus progestin substudy of WHI, a statistically significant increased risk of stroke was reported in women receiving daily CE 0.625 mg plus medroxyprogesterone acetate (MPA 2.5 mg) compared to placebo (31 versus 24 per 10,000 women-years). The increase in risk was demonstrated after the first year and persisted. (See CLINICAL STUDIES.)

b. Coronary heart disease

In the estrogen alone substudy of WHI, no overall effect on coronary heart disease (CHD) events (defined as nonfatal myocardial infarction [MI], silent MI, or CHD death) was reported in women receiving estrogen alone compared to placebo. (See CLINICAL STUDIES.)

In the estrogen plus progestin substudy of WHI, no statistically significant increase of CHD events was reported in women receiving CE/MPA compared to placebo (39 versus 33 per 10,000 women years). An increase in relative risk was demonstrated in year 1, and a trend toward decreasing relative risk was reported in years 2 through 5.

In postmenopausal women with documented heart disease (n = 2,763, average age 66.7 years), in a controlled clinical trial of secondary prevention of cardiovascular disease (Heart and Estrogen/progestin Replacement Study; HERS), treatment with daily CE 0.625 mg/MPA 2.5 mg demonstrated no cardiovascular benefit. During an average follow-up of 4.1 years, treatment with CE/MPA did not reduce the overall rate of CHD events in postmenopausal women with established coronary heart disease. There were more CHD events in the CE/MPA-treated group than in the placebo group in year one, but not during the subsequent years. Two thousand three hundred and twenty one (2,321) women from the original HERS trial agreed to participate in an open-label extension of HERS, HERS II. Average follow-up in HERS II was an additional 2.7 years, for a total of 6.8 years overall. Rates of CHD events were comparable among women in the CE/MPA group and the placebo group in the HERS, the HERS II, and overall.

c. Venous thromboembolism (VTE)

In the estrogen alone substudy of WHI, the risk of VTE (DVT and pulmonary embolism [PE]), was reported to be increased for women receiving daily CE compared to placebo (30 versus 22 per 10,000 women-years), although only the increased risk of DVT reached statistical significance (23 versus 15 per 10,000 women years). The increase in VTE risk was demonstrated during the first 2 years. (See CLINICAL STUDIES.)

In the estrogen plus progestin substudy of WHI, a statistically significant 2-fold greater rate of VTE was reported in women receiving daily CE/MPA compared to placebo (35 versus 17 per 10,000 women-years). Statistically significant increases in risk for both DVT (26 versus 13 per 10,000 women-years) and PE (18 versus 8 per 10,000 women years) were also demonstrated. The increase in VTE risk was demonstrated during the first year and persisted. (See CLINICAL STUDIES.)

If feasible, estrogens should be discontinued at least 4 to 6 weeks before surgery of the type associated with an increased risk of thromboembolism, or during periods of prolonged immobilization.

2. Malignant neoplasms

a. Endometrial cancer

An increased risk of endometrial cancer has been reported with the use of unopposed estrogen therapy in women with a uterus. The reported endometrial cancer risk among unopposed estrogen users with an intact uterus is about 2 to 12 times greater than in non-users, and appears dependent on duration of treatment and on estrogen dose. Most studies show no significant increased risk associated with the use of estrogens for less than 1 year. The greatest risk appears associated with prolonged use, with increased risks of 15- to 24-fold for 5 to 10 years or more, and this risk has been shown to persist for at least 8 to 15 years after estrogen therapy is discontinued.

Clinical surveillance of all women using estrogen plus progestin therapy is important. Adequate diagnostic measures, including endometrial sampling when indicated, should be undertaken to rule out malignancy in all cases of undiagnosed persistent or recurring abnormal vaginal bleeding. There is no evidence that the use of natural estrogens results in a different endometrial risk profile than synthetic estrogens of equivalent estrogen dose. Adding a progestin to postmenopausal estrogen therapy has been shown to reduce the risk of endometrial hyperplasia, which may be a precursor to endometrial cancer.

b. Breast cancer

The most important randomized clinical trial providing information about this issue in estrogen alone users is the Women's Health Initiative (WHI) substudy of daily conjugated estrogens (CE 0.625 mg). In the estrogen alone substudy of WHI, after an average 7.1 years of follow-up, daily CE 0.625 mg was not associated with an increased risk of invasive breast cancer (relative risk [RR] 0.80, 95 percent nominal confidence interval [nCI] 0.62-1.04). (see CLINICAL STUDIES).

The most important randomized clinical trial providing information about this issue in estrogen plus progestin users is the Women's Health Initiative (WHI) substudy of daily CE 0.625 mg plus medroxyprogesterone acetate (MPA 2.5 mg). In the estrogen plus progestin substudy, after a mean follow-up of 5.6 years, the WHI substudy reported an increased risk of breast cancer in women who took daily CE/MPA. In this substudy, prior use of estrogen alone or estrogen plus progestin therapy was reported by 26 percent of the women. The relative risk of invasive breast cancer was 1.24 (95 percent nCI 1.01-1.54), and the absolute risk was 41 versus 33 cases per 10,000 women-years, for estrogen plus progestin compared with placebo, respectively. Among women who reported prior use of hormone therapy, the relative risk of invasive breast cancer was 1.86, and the absolute risk was 46 versus 25 cases per 10,000 women-years, for CE/MPA compared with placebo. Among women who reported no prior use of hormone therapy, the relative risk of invasive breast cancer was 1.09, and the absolute risk was 40 versus 36 cases per 10,000 women-years for estrogen plus progestin compared with placebo. In the same substudy, invasive breast cancers were larger and diagnosed at a more advanced stage in the CE/MPA group compared with the placebo group. Metastatic disease was rare, with no apparent difference between the two groups. Other prognostic factors, such as histologic subtype, grade and hormone receptor status did not differ between the groups. (See CLINICAL STUDIES.)

The results from observational studies are generally consistent with those of the WHI clinical trial. Observational studies have also reported an increased risk of breast cancer for estrogen plus progestin therapy, and a smaller increased risk for estrogen alone therapy, after several years of use. The risk increased with duration of use, and appeared to return to baseline over about 5 years after stopping treatment (only the observational studies have substantial data on risk after stopping). Observational studies also suggest that the risk of breast cancer was greater, and became apparent earlier, with estrogen plus progestin therapy as compared to estrogen alone therapy. However, these studies have not found significant variation in the risk of breast cancer among different estrogen plus progestin combinations, doses, or routes of administration.

The use of estrogen alone and estrogen plus progestin has been reported to result in an increase in abnormal mammograms requiring further evaluation.

All women should receive yearly breast examinations by a healthcare provider and perform monthly breast self-examinations. In addition, mammography examinations should be scheduled based on patient age, risk factors, and prior mammogram results.

3. Dementia

In the estrogen alone Women's Health Initiative Memory Study (WHIMS), a substudy of WHI, a population of 2,947 hysterectomized women 65 to 79 years of age was randomized to daily conjugated estrogens (CE 0.625 mg) or placebo. In the estrogen plus progestin WHIMS substudy, a population of 4,532 postmenopausal women 65 to 79 years of age was randomized to daily CE 0.625 mg plus medroxyprogesterone acetate (MPA 2.5 mg) or placebo.

In the estrogen alone substudy, after an average follow-up of 5.2 years, 28 women in the estrogen alone group and 19 women in the placebo group were diagnosed with probable dementia. The relative risk of probable dementia for CE alone versus placebo was 1.49 (95 percent CI 0.83-2.66). The absolute risk of probable dementia for CE alone versus placebo was 37 versus 25 cases per 10,000 women-years. (See CLINICAL STUDIES and PRECAUTIONS, Geriatric Use.)

In the estrogen plus progestin substudy, after an average follow-up of 4 years, 40 women in the CE/MPA group and 21 women in the placebo group were diagnosed with probable dementia. The relative risk of probable dementia for CE/MPA versus placebo was 2.05 (95 percent CI 1.21-3.48). The absolute risk of probable dementia for CE/MPA versus placebo was 45 versus 22 cases per 10,000 women-years. (See CLINICAL STUDIES and PRECAUTIONS, Geriatric Use.)

When data from the two populations were pooled as planned in the WHIMS protocol, the reported overall relative risk for probable dementia was 1.76 (95 percent CI 1.19-2.60). Since both substudies were conducted in women 65 to 79 years of age, it is unknown whether these findings apply to younger postmenopausal women. (See BOXED WARNINGS and PRECAUTIONS, Geriatric Use.)

4. Gallbladder Disease

A 2- to 4-fold increase in the risk of gallbladder disease requiring surgery in postmenopausal women receiving estrogens has been reported.

5. Hypercalcemia

Estrogen administration may lead to severe hypercalcemia in patients with breast cancer and bone metastases. If hypercalcemia occurs, use of the drug should be stopped and appropriate measures taken to reduce the serum calcium level.

6. Visual abnormalities

Retinal vascular thrombosis has been reported in patients receiving estrogens. Discontinue medication pending examination if there is sudden partial or complete loss of vision, or a sudden onset of proptosis, diplopia, or migraine. If examination reveals papilledema or retinal vascular lesions, estrogens should be permanently discontinued.

7. Angioedema

Exogenous estrogens may induce or exacerbate symptoms of angioedema, particularly in women with hereditary angioedema.

PRECAUTIONS

A. General

1. Addition of a progestin when a woman has not had a hysterectomy

Studies of the addition of a progestin for 10 or more days of a cycle of estrogen administration, or daily with estrogen in a continuous regimen, have reported a lowered incidence of endometrial hyperplasia than would be induced by estrogen treatment alone. Endometrial hyperplasia may be a precursor to endometrial cancer.

There are, however, possible risks that may be associated with the use of progestins with estrogens compared to estrogen-alone regimens. These include: a possible increased risk of breast cancer, adverse effects on lipoprotein metabolism (lowering HDL, raising LDL) and impairment of glucose tolerance.

2. Elevated blood pressure

In a small number of case reports, substantial increases in blood pressure have been attributed to idiosyncratic reactions to estrogens. In a large, randomized, placebo-controlled clinical trial, a generalized effect of estrogen therapy on blood pressure was not seen. Blood pressure should be monitored at regular intervals during estrogen use.

3. Hypertriglyceridemia

In patients with pre-existing hypertriglyceridemia, estrogen therapy may be associated with elevations of plasma triglycerides leading to pancreatitis and other complications. Consider discontinuation of treatment if pancreatitis or other complications develop.

In the HOPE study, the mean percent increase from baseline in serum triglycerides after one year of treatment with PREMARIN 0.625 mg, 0.45 mg, and 0.3 mg compared with placebo were 34.3, 30.2, 25.1, and 10.7, respectively. After two years of treatment, the mean percent changes were 47.6, 32.5, 19.0, and 5.5, respectively.

4. Impaired liver function and past history of cholestatic jaundice

Estrogens may be poorly metabolized in patients with impaired liver function. For patients with a history of cholestatic jaundice associated with past estrogen use or with pregnancy, caution should be exercised, and in the case of recurrence, medication should be discontinued.

5. Hypothyroidism

Estrogen administration leads to increased thyroid-binding globulin (TBG) levels. Patients with normal thyroid function can compensate for the increased TBG by making more thyroid hormone, thus maintaining free T4 and T3 serum concentrations in the normal range. Patients dependent on thyroid hormone replacement therapy who are also receiving estrogens may require increased doses of their thyroid replacement therapy. These patients should have their thyroid function monitored in order to maintain their free thyroid hormone levels in an acceptable range.

6. Fluid retention

Estrogens may cause some degree of fluid retention. Patients with conditions that might be influenced by this factor, such as cardiac or renal dysfunction, warrant careful observation when estrogens are prescribed.

7. Hypocalcemia

Estrogens should be used with caution in individuals with severe hypocalcemia.

8. Ovarian cancer

The estrogen plus progestin substudy of WHI reported a non-statistically significant increased risk of ovarian cancer. After an average follow-up of 5.6 years, the relative risk for ovarian cancer for CE/MPA versus placebo was 1.58 (95 percent nCI 0.77 – 3.24). The absolute risk for CE/MPA versus placebo was 4.2 versus 2.7 cases per 10,000 women-years. In some epidemiologic studies, the use of estrogen-only products, in particular for 5 or more years, has been associated with an increased risk of ovarian cancer. However, the duration of exposure associated with increased risk is not consistent across all epidemiologic studies and some report no association.

9. Exacerbation of endometriosis

Endometriosis may be exacerbated with administration of estrogen therapy.

A few cases of malignant transformation of residual endometrial implants have been reported in women treated post-hysterectomy with estrogen alone therapy. For patients known to have residual endometriosis post-hysterectomy, the addition of progestin should be considered.

10. Exacerbation of other conditions

Estrogen therapy may cause an exacerbation of asthma, diabetes mellitus, epilepsy, migraine, porphyria, systemic lupus erythematosus, and hepatic hemangiomas and should be used with caution in patients with these conditions.

B. Patient Information

Physicians are advised to discuss the contents of the PATIENT INFORMATION leaflet with patients for whom they prescribe PREMARIN.

C. Laboratory Tests

Serum follicle stimulating hormone and estradiol levels have not been shown to be useful in the management of moderate to severe vasomotor symptoms and moderate to severe symptoms of vulvar and vaginal atrophy.

Laboratory parameters may be useful in guiding dosage for the treatment of hypoestrogenism due to hypogonadism, castration and primary ovarian failure.

D. Drug/Laboratory Test Interactions

1. Accelerated prothrombin time, partial thromboplastin time, and platelet aggregation time; increased platelet count; increased factors II, VII antigen, VIII antigen, VIII coagulant activity, IX, X, XII, VII-X complex, II-VII-X complex, and beta-thromboglobulin; decreased levels of anti-factor Xa and antithrombin III, decreased antithrombin III activity; increased levels of fibrinogen and fibrinogen activity; increased plasminogen antigen and activity.
2. Increased thyroid binding globulin (TBG) levels leading to increased circulating total thyroid hormone levels as measured by protein-bound iodine (PBI), T4 levels (by column or by radioimmunoassay) or T3 levels by radioimmunoassay. T3 resin uptake is decreased, reflecting the elevated TBG. Free T4 and free T3 concentrations are unaltered. Patients on thyroid replacement therapy may require higher doses of thyroid hormone.
3. Other binding proteins may be elevated in serum, i.e., corticosteroid binding globulin (CBG), sex hormone binding globulin (SHBG), leading to increased total circulating corticosteroids and sex steroids, respectively. Free hormone concentrations may be decreased. Other plasma proteins may be increased (angiotensinogen/renin substrate, alpha-1-antitrypsin, ceruloplasmin).
4. Increased plasma HDL and HDL2 cholesterol subfraction concentrations, reduced LDL cholesterol concentrations, increased triglyceride levels.
5. Impaired glucose tolerance.

E. Carcinogenesis, Mutagenesis, Impairment of Fertility

(See BOXED WARNINGS, WARNINGS, and PRECAUTIONS.)

Long-term continuous administration of natural and synthetic estrogens in certain animal species increases the frequency of carcinomas of the breast, uterus, cervix, vagina, testis, and liver.

F. Pregnancy

PREMARIN should not be used during pregnancy. (See CONTRAINDICATIONS.)

G. Nursing Mothers

PREMARIN should not be used during lactation. Estrogen administration to nursing mothers has been shown to decrease the quantity and quality of the milk. Detectable amounts of estrogens have been identified in the milk of mothers receiving this drug.

H. Pediatric Use

Estrogen therapy has been used for the induction of puberty in adolescents with some forms of pubertal delay. Safety and effectiveness in pediatric patients have not otherwise been established.

Large and repeated doses of estrogen over an extended time period have been shown to accelerate epiphyseal closure, which could result in short stature if treatment is initiated before the completion of physiologic puberty in normally developing children. If estrogen is administered to patients whose bone growth is not complete, periodic monitoring of bone maturation and effects on epiphyseal centers is recommended during estrogen administration.

Estrogen treatment of prepubertal girls also induces premature breast development and vaginal cornification, and may induce vaginal bleeding. In boys, estrogen treatment may modify the normal pubertal process and induce gynecomastia. (See INDICATIONS AND USAGE and DOSAGE AND ADMINISTRATION.)

I. Geriatric Use

With respect to efficacy in the approved indications, there have not been sufficient numbers of geriatric patients involved in studies utilizing PREMARIN to determine whether those over 65 years of age differ from younger subjects in their response to PREMARIN.

In the estrogen alone substudy of the Women's Health Initiative (WHI) study, 46 percent (n=4,943) were 65 years of age and older, while 7.1 percent (n=767) were 75 years of age and older. There was a higher relative risk (daily conjugated estrogens [CE 0.625 mg] versus placebo) of stroke in women less than 75 years of age compared to women 75 years and older.

In the estrogen alone Women's Health Initiative Memory Study (WHIMS), a substudy of WHI, a population of 2,947 hysterectomized women, 65 to 79 years of age, was randomized to daily CE 0.625 mg or placebo. After an average follow-up of 5.2 years, the relative risk (CE versus placebo) of probable dementia was 1.49 (95 percent CI 0.83-2.66). The absolute risk of developing probable dementia with estrogen alone was 37 versus 25 cases per 10,000 women-years compared with placebo.

Of the total number of subjects in the estrogen plus progestin substudy of the Women's Health Initiative study, 44 percent (n=7,320) were 65 years of age and older, while 6.6 percent (n=1,095) were 75 years and older. In women 75 years of age and older compared to women less than 74 years of age, there was a higher relative risk of nonfatal stroke and invasive breast cancer in the estrogen plus progestin group versus placebo. In women greater than 75, the increased risk of nonfatal stroke and invasive breast cancer observed in the estrogen plus progestin group compared to placebo was 75 versus 24 per 10,000 women-years and 52 versus 12 per 10,000 women years, respectively.

In the estrogen plus progestin substudy of WHIMS, a population of 4,532 postmenopausal women, 65 to 79 years of age, was randomized to daily CE 0.625 mg/MPA 2.5 mg or placebo. In the estrogen plus progestin group, after an average follow-up of 4 years, the relative risk (CE/MPA versus placebo) of probable dementia was 2.05 (95 percent CI 1.21-3.48). The absolute risk of developing probable dementia with CE/MPA was 45 versus 22 cases per 10,000 women-years compared with placebo.

Seventy-nine percent of the cases of probable dementia occurred in women that were older than 70 for the CE alone group, and 82 percent of the cases of probable dementia occurred in women who were older than 70 in the CE/MPA group. The most common classification of probable dementia in both the treatment groups and placebo groups was Alzheimer’s disease.

When data from the two populations were pooled as planned in the WHIMS protocol, the reported overall relative risk for probable dementia was 1.76 (95 percent CI 1.19-2.60). Since both substudies were conducted in women 65 to 79 years of age, it is unknown whether these findings apply to younger postmenopausal women. (See BOXED WARNINGS and WARNINGS, Dementia.)

ADVERSE REACTIONS

See BOXED WARNINGS, WARNINGS, and PRECAUTIONS.

Because clinical trials are conducted under widely varying conditions, adverse reaction rates observed in the clinical trials of a drug cannot be directly compared to rates in the clinical trials of another drug and may not reflect the rates observed in practice.

During the first year of a 2-year clinical trial with 2,333 postmenopausal women between 40 and 65 years of age (88% Caucasian), 1,012 women were treated with conjugated estrogens and 332 were treated with placebo. Table 6 summarizes adverse events that occurred at a rate of ≥ 5%.

TABLE 6. NUMBER (%) OF PATIENTS REPORTING ≥ 5% TREATMENT EMERGENT ADVERSE EVENTS
 | --Conjugated Estrogens Treatment Group--
Body System | 0.625 mg | 0.45 mg | 0.3 mg | Placebo
Adverse event | (n = 348) | (n = 338) | (n = 326) | (n = 332)
Any adverse event | 323 (93%) | 305 (90%) | 292 (90%) | 281 (85%)
Body as a Whole
Abdominal pain Accidental injury Asthenia Back pain Flu syndrome Headache Infection Pain | 56 (16%) 21 (6%) 25 (7%) 49 (14%) 37 (11%) 90 (26%) 61 (18%) 58 (17%) | 50 (15%) 41 (12%) 23 (7%) 43 (13%) 38 (11%) 109 (32%) 75 (22%) 61 (18%) | 54 (17%) 20 (6%) 25 (8%) 43 (13%) 33 (10%) 96 (29%) 74 (23%) 66 (20%) | 37 (11%) 29 (9%) 16 (5%) 39 (12%) 35 (11%) 93 (28%) 74 (22%) 61 (18%)
Digestive System
Diarrhea Dyspepsia Flatulence Nausea | 21 (6%) 33 (9%) 24 (7%) 32 (9%) | 25 (7%) 32 (9%) 23 (7%) 21 (6%) | 19 (6%) 36 (11%) 18 (6%) 21 (6%) | 21 (6%) 46 (14%) 9 (3%) 30 (9%)
Musculoskeletal System
Arthralgia Leg cramps Myalgia | 47 (14%) 19 (5%) 18 (5%) | 42 (12%) 23 (7%) 18 (5%) | 22 (7%) 11 (3%) 29 (9%) | 39 (12%) 7 (2%) 25 (8%)
Nervous System
Depression Dizziness Insomnia Nervousness | 25 (7%) 19 (5%) 21 (6%) 12 (3%) | 27 (8%) 20 (6%) 25 (7%) 17 (5%) | 17 (5%) 12 (4%) 24 (7%) 6 (2%) | 22 (7%) 17 (5%) 33 (10%) 7 (2%)
Respiratory System
Cough increased Pharyngitis Rhinitis Sinusitis Upper respiratory infection | 13 (4%) 35 (10%) 21 (6%) 22 (6%) 42 (12%) | 22 (7%) 35 (10%) 30 (9%) 36 (11%) 34 (10%) | 14 (4%) 40 (12%) 31 (10%) 24 (7%) 28 (9%) | 14 (4%) 38 (11%) 42 (13%) 24 (7%) 35 (11%)
Skin and Appendages
Pruritus | 14 (4%) | 17 (5%) | 16 (5%) | 7 (2%)
Urogenital System
Breast pain Leukorrhea Vaginal hemorrhage Vaginal moniliasis Vaginitis | 38 (11%) 18 (5%) 47 (14%) 20 (6%) 24 (7%) | 41 (12%) 22 (7%) 14 (4%) 18 (5%) 20 (6%) | 24 (7%) 13 (4%) 7 (2%) 17 (5%) 16 (5%) | 29 (9%) 9 (3%) 0 6 (2%) 4 (1%)

The following additional adverse reactions have been reported with estrogen and/or progestin therapy:

1. Genitourinary system

Abnormal uterine bleeding/spotting

Dysmenorrhea/pelvic pain

Increase in size of uterine leiomyomata

Vaginitis, including vaginal candidiasis

Change in amount of cervical secretion

Change in cervical ectropion

Ovarian cancer

Endometrial hyperplasia

Endometrial cancer

2. Breasts

Tenderness, enlargement, pain, discharge, galactorrhea

Fibrocystic breast changes

Breast cancer

3. Cardiovascular

Deep and superficial venous thrombosis

Pulmonary embolism

Thrombophlebitis

Myocardial infarction

Stroke

Increase in blood pressure

4. Gastrointestinal

Nausea, vomiting

Abdominal cramps, bloating

Cholestatic jaundice

Increased incidence of gallbladder disease

Pancreatitis

Enlargement of hepatic hemangiomas

Ischemic colitis

5. Skin

Chloasma or melasma that may persist when drug is discontinued

Erythema multiforme

Erythema nodosum

Hemorrhagic eruption

Loss of scalp hair

Hirsutism

Pruritus, rash

6. Eyes

Retinal vascular thrombosis

Intolerance to contact lenses

7. Central Nervous System

Headache

Migraine

Dizziness

Mental depression

Exacerbation of chorea

Nervousness

Mood disturbances

Irritability

Exacerbation of epilepsy

Dementia

Possible growth potentiation of benign meningioma

8. Miscellaneous

Increase or decrease in weight

Glucose intolerance

Aggravation of porphyria

Edema

Arthralgias

Leg cramps

Changes in libido

Urticaria, angioedema, anaphylactoid/anaphylactic reactions

Hypocalcemia (preexisting condition)

Exacerbation of asthma

Increased triglycerides

OVERDOSAGE

Overdosage of estrogen may cause nausea and vomiting, breast tenderness, abdominal pain, drowsiness/fatigue and withdrawal bleeding may occur in females. Treatment of overdose consists of discontinuation of PREMARIN together with institution of appropriate symptomatic care.

DOSAGE AND ADMINISTRATION

When estrogen is prescribed for a postmenopausal woman with a uterus, progestin should also be initiated to reduce the risk of endometrial cancer. A woman without a uterus does not need progestin. Use of estrogen, alone or in combination with a progestin, should be with the lowest effective dose and for the shortest duration consistent with treatment goals and risks for the individual woman. Patients should be reevaluated periodically as clinically appropriate (for example at 3-month to 6-month intervals) to determine if treatment is still necessary (see BOXED WARNINGS and WARNINGS). For women with a uterus, adequate diagnostic measures, such as endometrial sampling, when indicated, should be undertaken to rule out malignancy in cases of undiagnosed persistent or recurring abnormal vaginal bleeding.

PREMARIN may be taken without regard to meals.

1. For treatment of moderate to severe vasomotor symptoms and/or moderate to severe symptoms of vulvar and vaginal atrophy due to menopause:
  When prescribing solely for the treatment of moderate to severe symptoms of vulvar and vaginal atrophy, topical vaginal products should be considered.
  Patients should be treated with the lowest effective dose. Generally, women should be started at 0.3 mg PREMARIN daily. Subsequent dosage adjustment may be made based upon the individual patient response. This dose should be periodically reassessed by the healthcare provider.
  PREMARIN therapy may be given continuously, with no interruption in therapy, or in cyclical regimens (regimens such as 25 days on drug followed by five days off drug), as is medically appropriate on an individualized basis.
2. For prevention of postmenopausal osteoporosis:
  When prescribing solely for the prevention of postmenopausal osteoporosis, therapy should be considered only for women at significant risk of osteoporosis and for whom non-estrogen medications are not considered to be appropriate. Patients should be treated with the lowest effective dose. Generally, women should be started at 0.3 mg PREMARIN daily. Subsequent dosage adjustment may be made based upon the individual clinical and bone mineral density responses. This dose should be periodically reassessed by the healthcare provider.
  PREMARIN therapy may be given continuously, with no interruption in therapy, or in cyclical regimens (regimens such as 25 days on drug followed by five days off drug), as is medically appropriate on an individualized basis.
3. For treatment of female hypoestrogenism due to hypogonadism, castration, or primary ovarian failure:
  Female hypogonadism — 0.3 mg or 0.625 mg daily, administered cyclically (e.g., three weeks on and one week off). Doses are adjusted depending on the severity of symptoms and responsiveness of the endometrium.
  In clinical studies of delayed puberty due to female hypogonadism, breast development was induced by doses as low as 0.15 mg. The dosage may be gradually titrated upward at 6-to-12 month intervals as needed to achieve appropriate bone age advancement and eventual epiphyseal closure. Clinical studies suggest that doses of 0.15 mg, 0.3 mg, and 0.6 mg are associated with mean ratios of bone age advancement to chronological age progression (ΔBA/ΔCA) of 1.1, 1.5, and 2.1, respectively. (PREMARIN in the dose strength of 0.15 mg is not available commercially). Available data suggest that chronic dosing with 0.625 mg is sufficient to induce artificial cyclic menses with sequential progestin treatment and to maintain bone mineral density after skeletal maturity is achieved.
  Female castration or primary ovarian failure — 1.25 mg daily, cyclically. Adjust dosage, upward or downward, according to severity of symptoms and response of the patient. For maintenance, adjust dosage to lowest level that will provide effective control.
4. For treatment of breast cancer, for palliation only, in appropriately selected women and men with metastatic disease:
  Suggested dosage is 10 mg three times daily, for a period of at least three months.
5. For treatment of advanced androgen-dependent carcinoma of the prostate, for palliation only:
  1.25 mg to 2 x 1.25 mg three times daily. The effectiveness of therapy can be judged by phosphatase determinations as well as by symptomatic improvement of the patient.

HOW SUPPLIED

PREMARIN® (conjugated estrogens tablets, USP)

— Each oval yellow tablet contains 1.25 mg
— Each oval white tablet contains 0.9 mg
— Each oval maroon tablet contains 0.625 mg | in bottles of 10 in bottles of 30 | NDC 54868-0451-6 NDC 54868-0451-2
— Each oval blue tablet contains 0.45 mg
— Each oval green tablet contains 0.3 mg | in bottles of 10 in bottles of 30 | NDC 54868-2702-1 NDC 54868-2702-0

The appearance of these tablets is a trademark of Wyeth Pharmaceuticals.

Store at 20°-25°C (68°-77°F); excursions permitted to 15°-30°C (59°-86°F) [see USP Controlled Room Temperature].

Dispense in a well-closed container, as defined in the USP.

PATIENT INFORMATION

PREMARIN®

(conjugated estrogens tablets, USP)

Read this PATIENT INFORMATION before you start taking PREMARIN and read what you get each time you refill your PREMARIN prescription. There may be new information. This information does not take the place of talking to your healthcare provider about your medical condition or your treatment.

What is the most important information I should know about PREMARIN (an estrogen mixture)?

- Estrogens increase the chance of getting cancer of the uterus.
  Report any unusual vaginal bleeding right away while you are taking PREMARIN. Vaginal bleeding after menopause may be a warning sign of cancer of the uterus (womb). Your healthcare provider should check any unusual vaginal bleeding to find out the cause.
- Do not use estrogens with or without progestins to prevent heart disease, heart attacks, strokes, or dementia.
  Using estrogens, with or without progestins, may increase your chance of getting heart attacks, strokes, breast cancer, and blood clots. Using estrogens, with or without progestins, may increase your chance of getting dementia, based on a study of women age 65 years or older. You and your healthcare provider should talk regularly about whether you still need treatment with PREMARIN.

What is PREMARIN?

PREMARIN is a medicine that contains a mixture of estrogen hormones.

PREMARIN is used after menopause to:

- Reduce moderate to severe hot flashes. Estrogens are hormones made by a woman's ovaries. The ovaries normally stop making estrogens when a woman is between 45 and 55 years old. This drop in body estrogen levels causes the “change of life” or menopause (the end of monthly menstrual periods). Sometimes both ovaries are removed during an operation before natural menopause takes place. The sudden drop in estrogen levels causes “surgical menopause.”
  When the estrogen levels begin dropping, some women get very uncomfortable symptoms, such as feelings of warmth in the face, neck, and chest, or sudden strong feelings of heat and sweating (“hot flashes” or “hot flushes”). In some women the symptoms are mild, and they will not need to take estrogens. In other women, symptoms can be more severe. You and your healthcare provider should talk regularly about whether you still need treatment with PREMARIN.
- Treat moderate to severe dryness, itching, and burning, in and around the vagina. You and your healthcare provider should talk regularly about whether you still need treatment with PREMARIN to control these problems. If you use PREMARIN only to treat your dryness, itching, and burning in and around your vagina, talk with your healthcare provider about whether a topical vaginal product would be better for you.
- Help reduce your chances of getting osteoporosis (thin weak bones). Osteoporosis from menopause is a thinning of the bones that makes them weaker and easier to break. If you use PREMARIN only to prevent osteoporosis due to menopause, talk with your healthcare provider about whether a different treatment or medicine without estrogens might be better for you. You and your healthcare provider should talk regularly about whether you should continue with PREMARIN.
  Weight-bearing exercise, like walking or running, and taking calcium and vitamin D supplements may also lower your chances for getting postmenopausal osteoporosis. It is important to talk about exercise and supplements with your healthcare provider before starting them.

PREMARIN is also used to:

- Treat certain conditions in women before menopause if their ovaries do not make enough estrogen naturally.
- Ease symptoms of certain cancers that have spread through the body, in men and women.

Who should not take PREMARIN?

Do not start taking PREMARIN if you:

- Have unusual vaginal bleeding.
- Currently have or have had certain cancers. Estrogens may increase the chance of getting certain types of cancers, including cancer of the breast or uterus. If you have or have had cancer, talk with your healthcare provider about whether you should take PREMARIN.
- Had a stroke or heart attack in the past year.
- Currently have or have had blood clots.
- Currently have or have had liver problems.
- Are allergic to PREMARIN tablets or any of its ingredients. See the list of ingredients in PREMARIN at the end of this leaflet.
- Think you may be pregnant.

Tell your healthcare provider:

- If you are breast feeding. The hormones in PREMARIN can pass into your milk.
- About all of your medical problems. Your healthcare provider may need to check you more carefully if you have certain conditions, such as asthma (wheezing), epilepsy (seizures), migraine, endometriosis, lupus, problems with your heart, liver, thyroid, kidneys, or have high calcium levels in your blood.
- About all the medicines you take, including prescription and nonprescription medicines, vitamins, and herbal supplements. Some medicines may affect how PREMARIN works. PREMARIN may also affect how your other medicines work.
- If you are going to have surgery or will be on bedrest. You may need to stop taking estrogens.

How should I take PREMARIN?

- Take one PREMARIN tablet at the same time each day.
- If you miss a dose, take it as soon as possible. If it is almost time for your next dose, skip the missed dose and go back to your normal schedule. Do not take 2 doses at the same time.
- Estrogens should be used at the lowest dose possible for your treatment only as long as needed. You and your healthcare provider should talk regularly (for example, every 3 to 6 months) about the dose you are taking and whether you still need treatment with PREMARIN.

What are the possible side effects of PREMARIN?

Side effects are grouped by how serious they are and how often they happen when you are treated. Serious but less common side effects include:

- Breast cancer
- Cancer of the uterus
- Stroke
- Heart attack
- Blood clots
- Dementia
- Gallbladder disease
- Ovarian cancer
- High blood pressure
- Liver problems
- High blood sugar
- Enlargement of benign tumors of the uterus (“fibroids”)

Some of the warning signs of these serious side effects include:

- Breast lumps
- Unusual vaginal bleeding
- Dizziness and faintness
- Changes in speech
- Severe headaches
- Chest pain
- Shortness of breath
- Pains in your legs
- Changes in vision
- Vomiting
- Yellowing of the skin, eyes or nail beds

Call your healthcare provider right away if you get any of these warning signs, or any other unusual symptoms that concern you.

Less serious but common side effects include:

- Headache
- Breast pain
- Irregular vaginal bleeding or spotting
- Stomach/abdominal cramps, bloating
- Nausea and vomiting
- Hair loss
- Fluid retention
- Vaginal yeast infection

These are not all the possible side effects of PREMARIN. For more information, ask your healthcare provider or pharmacist.

What can I do to lower my chances of getting a serious side effect with PREMARIN?

- Talk with your healthcare provider regularly about whether you should continue taking PREMARIN.
- If you have a uterus, talk to your healthcare provider about whether the addition of a progestin is right for you. The addition of a progestin is generally recommended for women with a uterus to reduce the chance of getting cancer of the uterus.
- See your healthcare provider right away if you get vaginal bleeding while taking PREMARIN.
- Have a breast exam and mammogram (breast X-ray) every year unless your healthcare provider tells you something else. If members of your family have had breast cancer or if you have ever had breast lumps or an abnormal mammogram, you may need to have breast exams more often.
- If you have high blood pressure, high cholesterol (fat in the blood), diabetes, are overweight, or if you use tobacco, you may have higher chances for getting heart disease. Ask your healthcare provider for ways to lower your chances for getting heart disease.

General information about the safe and effective use of PREMARIN

Medicines are sometimes prescribed for conditions that are not mentioned in patient information leaflets. Do not take PREMARIN for conditions for which it was not prescribed. Do not give PREMARIN to other people, even if they have the same symptoms you have. It may harm them.

Keep PREMARIN out of the reach of children.

This leaflet provides a summary of the most important information about PREMARIN. If you would like more information, talk with your healthcare provider or pharmacist. You can ask for information about PREMARIN that is written for health professionals. You can get more information by calling the toll free number 800-934-5556.

What are the ingredients in PREMARIN?

PREMARIN contains a mixture of conjugated estrogens, which are a mixture of sodium estrone sulfate and sodium equilin sulfate and other components including sodium sulfate conjugates, 17 α-dihydroequilin, 17 α-estradiol, and 17 β-dihydroequilin.

PREMARIN 0.3 mg, 0.45 mg, 0.625 mg, 0.9 mg, and 1.25 mg tablets also contain the following inactive ingredients: calcium phosphate tribasic, hydroxypropyl cellulose, microcrystalline cellulose, powdered cellulose, hypromellose, lactose monohydrate, magnesium stearate, polyethylene glycol, sucrose and titanium dioxide.

The tablets come in different strengths and each strength tablet is a different color. The color ingredients are:

— 0.3 mg tablet (green color): D&C Yellow No. 10 and FD&C Blue No. 2.

— 0.45 mg tablet (blue color): FD&C Blue No. 2.

— 0.625 mg tablet (maroon color): FD&C Blue No. 2 and FD&C Red No. 40.

— 0.9 mg tablet (white color): D&C Red No. 30 and D&C Red No. 7.

— 1.25 mg tablet (yellow color): black iron oxide, D&C Yellow No. 10, and FD&C Yellow No. 6.

The appearance of these tablets is a trademark of Wyeth Pharmaceuticals.

Store at Controlled Room Temperature 20° – 25°C (68° – 77°F).

Wyeth®

Wyeth Pharmaceuticals Inc.

Philadelphia, PA 19101

W10405C025

ET01

Rev 02/10

PRINCIPAL DISPLAY PANEL

PREMARIN®

(conjugated estrogens tablets, USP)

0.3 mg

PREMARIN®

(conjugated estrogens tablets, USP)

0.45 mg

PREMARIN®

(conjugated estrogens tablets, USP)

0.3 mg

PREMARIN®

(conjugated estrogens tablets, USP)

0.625 mg

PREMARIN®

(conjugated estrogens tablets, USP)

0.9 mg

PREMARIN®

(conjugated estrogens tablets, USP)

1.25 mg